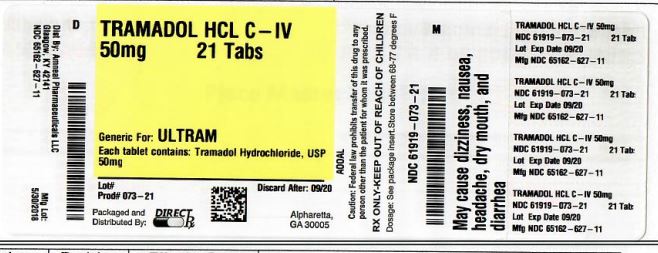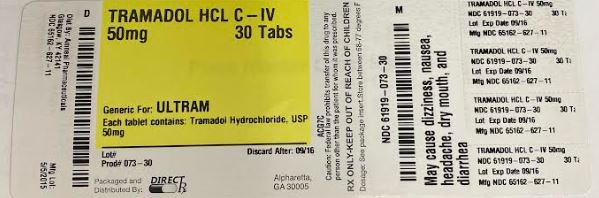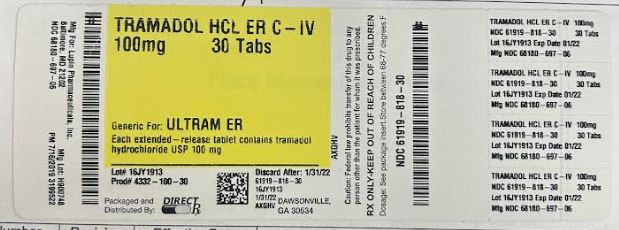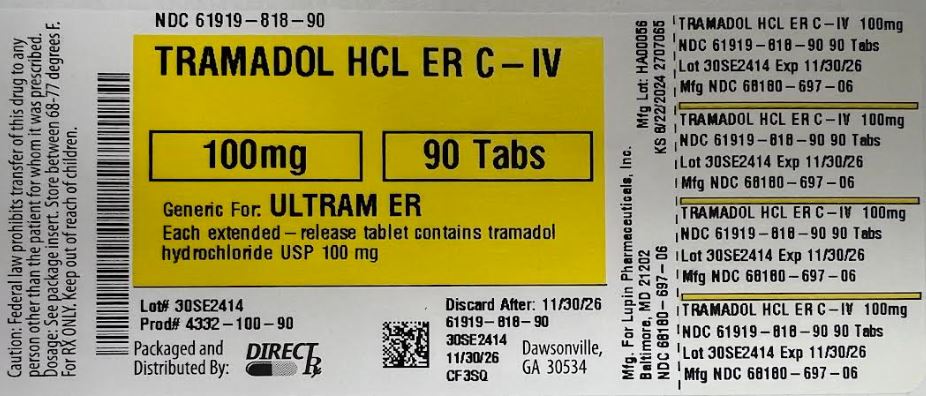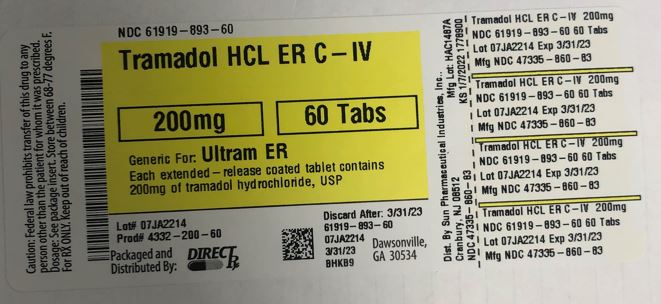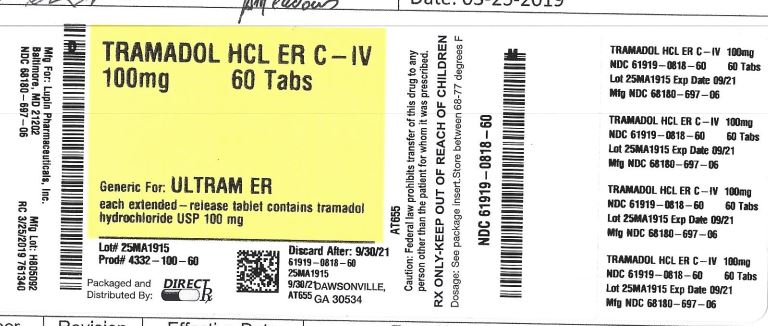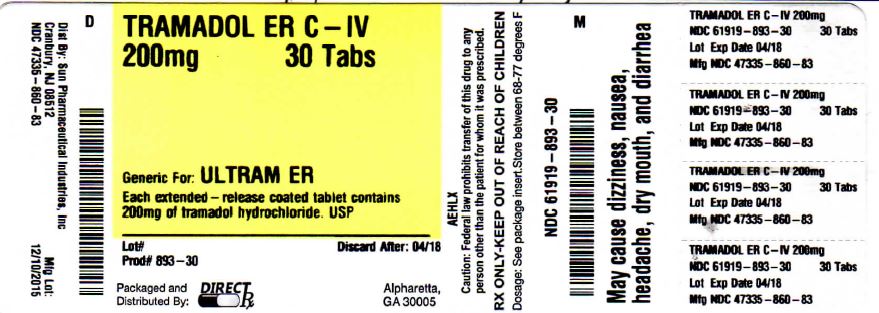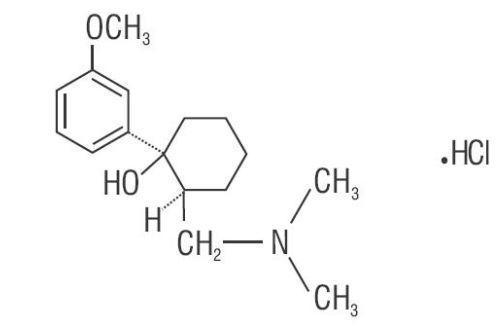 DRUG LABEL: TRAMADOL HCL
NDC: 61919-818 | Form: TABLET, EXTENDED RELEASE
Manufacturer: DIRECT RX
Category: prescription | Type: HUMAN PRESCRIPTION DRUG LABEL
Date: 20241017
DEA Schedule: CIV

ACTIVE INGREDIENTS: TRAMADOL HYDROCHLORIDE 100 mg/1 1
INACTIVE INGREDIENTS: DIBUTYL SEBACATE; ETHYLCELLULOSES; SHELLAC; CELLULOSE, MICROCRYSTALLINE; FERROSOFERRIC OXIDE; POVIDONE; PROPYLENE GLYCOL; SILICON DIOXIDE; SODIUM STEARYL FUMARATE

TRAMADOL HYDROCHLORIDE

DESCRIPTION SECTION

Tramadol hydrochloride is a centrally acting synthetic analgesic in an extended-release formulation. The chemical name is (±)cis-2-[(dimethylamino) methyl]-1-(3-methoxyphenyl) cyclohexanol hydrochloride. Its structural formula is:

Figure 1

The molecular weight of tramadol hydrochloride is 299.84. It is a white, crystalline powder that is freely soluble in water and methanol, very slightly soluble in acetone and has a pKa of 9.41. The n-octanol/water log partition coefficient (logP) is 1.35 at pH 7. Tramadol hydrochloride extended-release tablets contain 100 mg, 200 mg or 300 mg of tramadol hydrochloride, USP in an extended-release formulation. The tablets are white in color and contain the inactive ingredients pregelatinized maize starch, hypromellose, mannitol, magnesium stearate, cellulose acetate and polyethylene glycol.

Imprinting ink contains, shellac glaze, iron oxide black, N-butyl alcohol, ammonium hydroxide and propylene glycol.

CLINICAL PHARMACOLOGY SECTION

12.1 Mechanism of Action

Tramadol hydrochloride tablets contains tramadol, an opioid agonist and inhibitor of norepinephrine and serotonin re-uptake. Although the mode of action is not completely understood, the analgesic effect of tramadol is believed to be due to both binding to μ-opioid receptors and weak inhibition of re-uptake of norepinephrine and serotonin.

Opioid activity is due to both low affinity binding of the parent compound and higher affinity binding of the O-demethylated metabolite M1 to μ-opioid receptors. In animal models, M1 is up to 6 times more potent than tramadol in producing analgesia and 200 times more potent in μ-opioid binding. Tramadol-induced analgesia is only partially antagonized by the opioid antagonist naloxone in several animal tests. The relative contribution of both tramadol and M1 to human analgesia is dependent upon the plasma concentrations of each compound [see CLINICAL PHARMACOLOGY (12.2)].

Analgesia in humans begins approximately within one hour after administration and reaches a peak in approximately two to three hours.

12.2 Pharmacodynamics

Effects on the Central Nervous System

Tramadol produces respiratory depression by direct action on brain stem respiratory centers. The respiratory depression involves a reduction in the responsiveness of the brain stem respiratory centers to both increases in carbon dioxide tension and electrical stimulation.

Tramadol administration may produce a constellation of symptoms including nausea and vomiting, dizziness, and somnolence.

Tramadol causes miosis, even in total darkness. Pinpoint pupils are a sign of opioid overdose but are not pathognomonic (e.g., pontine lesions of hemorrhagic or ischemic origins may produce similar findings). Marked mydriasis rather than miosis may be seen due to hypoxia in overdose situations.

Effects on the Gastrointestinal Tract and Other Smooth Muscle

Tramadol causes a reduction in motility associated with an increase in smooth muscle tone in the antrum of the stomach and duodenum. Digestion of food in the small intestine is delayed and propulsive contractions are decreased. Propulsive peristaltic waves in the colon are decreased, while tone may be increased to the point of spasm resulting in constipation. Other opioid-induced effects may include a reduction in biliary and pancreatic secretions, spasm of sphincter of Oddi, and transient elevations in serum amylase.

Effects on the Cardiovascular System

Tramadol produces peripheral vasodilation, which may result in orthostatic hypotension or syncope. Manifestations of peripheral vasodilation may include pruritus, flushing, red eyes, sweating and/or orthostatic hypotension.

The effect of oral tramadol on the QTcF interval was evaluated in a double-blind, randomized, four-way crossover, placebo- and positive- (moxifloxacin) controlled study in 68 adult male and female healthy subjects. At a 600 mg/day dose (1.5-fold the maximum immediate-release daily dose), the study demonstrated no significant effect on the QTcF interval.

Effects on the Endocrine System

Opioids inhibit the secretion of adrenocorticotropic hormone (ACTH), cortisol, and luteinizing hormone (LH) in humans. They also stimulate prolactin, growth hormone (GH) secretion, and pancreatic secretion of insulin and glucagon [see WARNINGS AND PRECAUTIONS (5.11); Adverse Reactions (6)].

Chronic use of opioids may influence the hypothalamic-pituitary-gonadal axis, leading to androgen deficiency that may manifest as low libido, impotence, erectile dysfunction, amenorrhea, or infertility. The causal role of opioids in the clinical syndrome of hypogonadism is unknown because the various medical, physical, lifestyle, and psychological stressors that may influence gonadal hormone levels have not been adequately controlled for in studies conducted to date [see Adverse Reactions (6)].

Effects on the Immune System

Opioids have been shown to have a variety of effects on components of the immune system in in vitro and animal models. The clinical significance of these findings is unknown. Overall, the effects of opioids appear to be modestly immunosuppressive.

Concentration–Efficacy Relationships

The minimum effective analgesic concentration will vary widely among patients, especially among patients who have been previously treated with potent opioid agonists. The minimum effective analgesic concentration of tramadol for any individual patient may increase over time due to an increase in pain, the development of a new pain syndrome and/or the development of analgesic tolerance [see Dosage and Administration (2)].

Concentration–Adverse Reaction Relationships

There is a relationship between increasing tramadol plasma concentration and increasing frequency of dose-related opioid adverse reactions such as nausea, vomiting, CNS effects, and respiratory depression. In opioid-tolerant patients, the situation may be altered by the development of tolerance to opioid-related adverse reactions [see Dosage and Administration (2)].

12.3 Pharmacokinetics

The analgesic activity of tramadol hydrochloride is due to both parent drug and the M1 metabolite [see Clinical Pharmacology (12.1, 12.2)]. Tramadol is administered as a racemate and both the [-] and [+] forms of both tramadol and M1 are detected in the circulation. Linear pharmacokinetics have been observed following multiple doses of 50 and 100 mg to steady-state.

Absorption

The mean absolute bioavailability of a 100 mg oral dose is approximately 75%. The mean peak plasma concentration of racemic tramadol and M1 occurs at two and three hours, respectively, after administration in healthy adults. In general, both enantiomers of tramadol and M1 follow a parallel time course in the body following single and multiple doses although small differences (~ 10%) exist in the absolute amount of each enantiomer present.

Steady-state plasma concentrations of both tramadol and M1 are achieved within two days with four times per day dosing. There is no evidence of self-induction (see Figure 1 and Table 3 below).

Figure 1: Mean Tramadol and M1 Plasma Concentration Profiles after a Single 100 mg Oral Dose and after Twenty-Nine 100 mg Oral Doses of Tramadol Hydrochloride given four times per day.

[10]

Table 3: Mean (%CV) Pharmacokinetic Parameters for Racemic Tramadol and M1 Metabolite

Population/Dosage

Regimena

Parent Drug/

Metabolite

Peak Conc.(ng/mL)

Time to Peak

(hrs)

Clearance/Fb

(mL/min/Kg)

t1/2 (hrs)

Healthy Adults,

Tramadol

592 (30)

2.3 (61)

5.90 (25)c

6.7 (15)

100 mg qid, MD p.o.

M1

110 (29)

2.4 (46)

7.0 (14)

Healthy Adults,

Tramadol

308 (25)

1.6 (63)

8.50 (31)c

5.6 (20)

100 mg SD p.o.

M1

55.0 (36)

3.0 (51)

6.7 (16)

Geriatric, (>75 yrs)

Tramadol

208 (31)d

2.1 (19)d

6.89 (25)c

7.0 (23)d

50 mg SD p.o.

M1

Hepatic Impaired,

Tramadol

217 (11)

1.9 (16)

4.23 (56)c

13.3 (11)

50 mg SD p.o.

M1

19.4 (12)

9.8 (20)

18.5 (15)

Renal Impaired,

Tramadol

c

c

4.23 (54)c

10.6 (31)

CLcr10-30 mL/min

M1

c

c

11.5 (40)

100 mg SD i.v.

Renal Impaired,

Tramadol

c

c

3.73 (17)c

11.0 (29)

CLcr<5 mL/min

M1

c

c

16.9 (18)

100 mg SD i.v.

a SD = Single dose, MD = Multiple dose, p.o.= Oral administration, i.v.= Intravenous administration, q.i.d. = Four times daily

b F represents the oral bioavailability of tramadol

c Not applicable

d Not measured

Food Effects

Oral administration of tramadol hydrochloride with food does not significantly affect its rate or extent of absorption, therefore, tramadol hydrochloride can be administered without regard to food.

Distribution

The volume of distribution of tramadol was 2.6 and 2.9 liters/kg in male and female subjects, respectively, following a 100 mg intravenous dose. The binding of tramadol to human plasma proteins is approximately 20% and binding also appears to be independent of concentration up to 10 mcg/mL. Saturation of plasma protein binding occurs only at concentrations outside the clinically relevant range.

Elimination

Tramadol is eliminated primarily through metabolism by the liver and the metabolites are eliminated primarily by the kidneys. The mean (%CV) apparent total clearance of tramadol after a single 100 mg oral dose is 8.50 (31) mL/min/kg. The mean terminal plasma elimination half-lives of racemic tramadol and racemic M1 are 6.3 ± 1.4 and 7.4 ± 1.4 hours, respectively. The plasma elimination half-life of racemic tramadol increased from approximately six hours to seven hours upon multiple dosing.

Metabolism

Tramadol is extensively metabolized after oral administration by a number of pathways, including CYP2D6 and CYP3A4, as well as by conjugation of parent and metabolites. Approximately 30% of the dose is excreted in the urine as unchanged drug, whereas 60% of the dose is excreted as metabolites. The remainder is excreted either as unidentified or as unextractable metabolites. The major metabolic pathways appear to be N- and O-demethylation and glucuronidation or sulfation in the liver. One metabolite (O-desmethyltramadol, denoted M1) is pharmacologically active in animal models. Formation of M1 is dependent on CYP2D6 and as such is subject to inhibition, which may affect the therapeutic response [WARNINGS AND PRECAUTIONS (5.4); Drug Interactions (7)].

Approximately 7% of the population has reduced activity of the CYP2D6 isoenzyme of cytochrome P-450. These individuals are “poor metabolizers” of debrisoquine, dextromethorphan, tricyclic antidepressants, among other drugs. Based on a population PK analysis of Phase 1 studies in healthy subjects, concentrations of tramadol were approximately 20% higher in “poor metabolizers” versus “extensive metabolizers”, while M1 concentrations were 40% lower. Concomitant therapy with inhibitors of CYP2D6 such as fluoxetine, paroxetine and quinidine could result in significant drug interactions. In vitro drug interaction studies in human liver microsomes indicate that inhibitors of CYP2D6 such as fluoxetine and its metabolite norfluoxetine, amitriptyline and quinidine inhibit the metabolism of tramadol to various degrees, suggesting that concomitant administration of these compounds could result in increases in tramadol concentrations and decreased concentrations of M1. The full pharmacological impact of these alterations in terms of either efficacy or safety is unknown. Concomitant use of serotonin re-uptake inhibitors and MAO inhibitors may enhance the risk of adverse events, including seizure and serotonin syndrome [see WARNINGS AND PRECAUTIONS (5.8) and Drug Interactions (7)].

Excretion

Tramadol metabolites are eliminated primarily by the kidneys. Approximately 30% of the dose is excreted in the urine as unchanged drug, whereas 60% of the dose is excreted as metabolites. The remainder is excreted either as unidentified or as unextractable metabolites.

Special Populations

Hepatic Impairment

Metabolism of tramadol and M1 is reduced in patients with severe hepatic impairment based on a study in patients with advanced cirrhosis of the liver, resulting in both a larger area under the concentration time curve for tramadol and longer tramadol and M1 elimination half-lives (13 hrs. for tramadol and 19 hrs. for M1). In patients with severe hepatic impairment, adjustment of the dosing regimen is recommended [see Dosage and Administration (2)].

Renal Impairment

Impaired renal function results in a decreased rate and extent of excretion of tramadol and its active metabolite, M1. In patients with creatinine clearances of less than 30 mL/min, adjustment of the dosing regimen is recommended [see Dosage and Administration (2)]. The total amount of tramadol and M1 removed during a 4-hour dialysis period is less than 7% of the administered dose.

Age: Geriatric

Healthy elderly subjects aged 65 to 75 years have plasma tramadol concentrations and elimination half-lives comparable to those observed in healthy subjects less than 65 years of age. In subjects over 75 years, maximum serum concentrations are elevated (208 vs. 162 ng/mL) and the elimination half-life is prolonged (7 vs. 6 hours) compared to subjects 65 to 75 years of age. Adjustment of the daily dose is recommended for patients older than 75 years [see DOSAGE AND ADMINISTRATION (2.3)].

Sex

The absolute bioavailability of tramadol was 73% in males and 79% in females. The plasma clearance was 6.4 mL/min/kg in males and 5.7 mL/min/kg in females following a 100 mg IV dose of tramadol. Following a single oral dose, and after adjusting for body weight, females had a 12% higher peak tramadol concentration and a 35% higher area under the concentration-time curve compared to males. The clinical significance of this difference is unknown.

Poor / Extensive Metabolizers, CYP2D6

The formation of the active metabolite, M1, is mediated by CYP2D6, a polymorphic enzyme. Approximately 7% of the population has reduced activity of the CYP2D6 isoenzyme of cytochrome P450 metabolizing enzyme system. These individuals are “poor metabolizers” of debrisoquine, dextromethorphan and tricyclic antidepressants, among other drugs. Based on a population PK analysis of Phase 1 studies with IR tablets in healthy subjects, concentrations of tramadol were approximately 20% higher in “poor metabolizers” versus “extensive metabolizers,” while M1 concentrations were 40% lower.

CLINICAL STUDIES SECTION

- Tramadol hydrochloride was studied in patients with chronic, moderate to moderately severe pain due to osteoarthritis and/or low back pain in four 12-week, randomized, double-blind, placebo-controlled trials. To qualify for inclusion into these studies, patients were required to have moderate to moderately severe pain as defined by a pain intensity score of ≥40 mm, off previous medications, on a 0 mm to 100 mm visual analog scale (VAS). Adequate evidence of efficacy was demonstrated in the following two studies:
  In one 12-week randomized, double-blind, placebo-controlled study, patients with moderate to moderately severe pain due to osteoarthritis of the knee and/or hip were administered doses from 100 mg to 400 mg daily. Treatment was initiated at 100 mg QD for four days then increased by 100 mg per day increments every five days to the randomized fixed dose. Between 51% and 59% of patients in the tramadol hydrochloride extended-release tablets treatment groups completed the study and 56% of patients in the placebo group completed the study. Discontinuations due to adverse events were more common in the tramadol hydrochloride extended-release tablets 200 mg, 300 mg and 400 mg treatment groups (20%, 27%, and 30% of discontinuations, respectively) compared to 14% of the patients treated with tramadol hydrochloride extended-release tablets 100 mg and 20% of patients treated with placebo.
  Pain, as assessed by the WOMAC Pain subscale, was measured at 1, 2, 3, 6, 9, and 12 weeks and change from baseline assessed. A responder analysis based on the percent change in WOMAC Pain subscale demonstrated a statistically significant improvement in pain for the 100 mg and 200 mg treatment groups compared to placebo (see Figure 3).
  In one 12-week randomized, double-blind, placebo-controlled flexible-dosing trial of tramadol hydrochloride extended-release tablets in patients with osteoarthritis of the knee, patients titrated to an average daily tramadol hydrochloride extended-release tablets dose of approximately 270 mg/day. Forty-nine percent of patients randomized to tramadol hydrochloride extended-release tablets completed the study, while 52% of patients randomized to placebo completed the study. Most of the early discontinuations in the tramadol hydrochloride extended-release tablets treatment group were due to adverse events, accounting for 27% of the early discontinuations in contrast to 7% of the discontinuations from the placebo group.
  Thirty-four percent of the placebo-treated patients discontinued the study due to lack of efficacy compared to 15% of tramadol hydrochloride extended-release tablets-treated patients. The tramadol hydrochloride extended-release tablets group demonstrated a statistically significant decrease in the mean VAS score, and a statistically significant difference in the responder rate, based on the percent change from baseline in the VAS score, measured at 1, 2, 4, 8, and 12 weeks, between patients receiving tramadol hydrochloride extended-release tablets and placebo (see Figure 4).
  Close

INDICATIONS & USAGE SECTION

Tramadol hydrochloride extended-release tablets are indicated for the management of moderate to moderately severe chronic pain in adults who require around-the-clock treatment of their pain for an extended period of time

CONTRAINDICATIONS SECTION

Tramadol hydrochloride extended-release tablets should not be administered to patients who have previously demonstrated hypersensitivity to tramadol, any other component of this product or opioids. Tramadol hydrochloride extended-release tablets are contraindicated in any situation where opioids are contraindicated, including acute intoxication with any of the following: alcohol, hypnotics, narcotics, centrally acting analgesics, opioids or psychotropic drugs. Tramadol hydrochloride extended-release tablets may worsen central nervous system and respiratory depression in these patients.

WARNINGS SECTION

- Seizure Risk
  Seizures have been reported in patients receiving tramadol within the recommended dosage range. Spontaneous postmarketing reports indicate that seizure risk is increased with doses of tramadol above the recommended range. Concomitant use of tramadol increases the seizure risk in patients taking:
  - Selective serotonin re-uptake inhibitors (SSRI antidepressants or anorectics),
  - Tricyclic antidepressants (TCAs), and other tricyclic compounds (e.g., cyclobenzaprine, promethazine, etc.), or
  - Other opioids.
  Administration of tramadol may enhance the seizure risk in patients taking:
  - MAO inhibitors (see also WARNINGS - Use with MAO Inhibitors),
  - Neuroleptics, or
  - Other drugs that reduce the seizure threshold.
  Risk of convulsions may also increase in patients with epilepsy, those with a history of seizures, or in patients with a recognized risk for seizure (such as head trauma, metabolic disorders, alcohol and drug withdrawal, CNS infections). In tramadol overdose, naloxone administration may increase the risk of seizure.
  Suicide Risk
  - Do not prescribe tramadol hydrochloride extended-release tablets for patients who are suicidal or addiction-prone.
  - Prescribe tramadol hydrochloride extended-release tablets with caution for patients taking tranquilizers or antidepressant drugs and patients who use alcohol in excess.
  - Tell your patients not to exceed the recommended dose and to limit their intake of alcohol.
  Serotonin Syndrome Risk
  The development of a potentially life-threatening serotonin syndrome may occur with use of tramadol products, including tramadol hydrochloride extended-release tablets, particularly with concomitant use of serotonergic drugs such as SSRIs, SNRIs, TCAs, MAOIs and triptans, with drugs which impair metabolism of serotonin (including MAOIs) and with drugs which impair metabolism of tramadol (CYP2D6 and CYP3A4 inhibitors). This may occur within the recommended dose. (See CLINICAL PHARMACOLOGY - Pharmacokinetics).
  Serotonin syndrome may include mental-status changes (e.g., agitation, hallucinations, coma), autonomic instability (e.g., tachycardia, labile blood pressure, hyperthermia), neuromuscular aberrations (e.g., hyperreflexia, incoordination) and/or gastrointestinal symptoms (e.g., nausea, vomiting, diarrhea).
  Tramadol products in excessive doses, either alone or in combination with other CNS depressants, including alcohol, are a major cause of drug-related deaths. Fatalities within the first hour of overdosage are not uncommon. Tramadol should not be taken in doses higher than those recommended by the physician. The judicious prescribing of tramadol is essential to the safe use of this drug. With patients who are depressed or suicidal, consideration should be given to the use of non-narcotic analgesics. Patients should be cautioned about the concomitant use of tramadol products and alcohol because of potentially serious CNS-additive effects of these agents. Because of its added depressant effects, tramadol should be prescribed with caution for those patients whose medical condition requires the concomitant administration of sedatives, tranquilizers, muscle relaxants, antidepressants, or other CNS-depressant drugs. Patients should be advised of the additive depressant effects of these combinations.
  Many of the tramadol-related deaths have occurred in patients with previous histories of emotional disturbances or suicidal ideation or attempts as well as histories of misuse of tranquilizers, alcohol, and other CNS-active drugs. Some deaths have occurred as a consequence of the accidental ingestion of excessive quantities of tramadol alone or in combination with other drugs. Patients taking tramadol should be warned not to exceed the dose recommended by their physician.
  Anaphylactoid Reactions
  Serious and rarely fatal anaphylactoid reactions have been reported in patients receiving therapy with tramadol. When these events do occur it is often following the first dose. Other reported allergic reactions include pruritus, hives, bronchospasm, angioedema, toxic epidermal necrolysis and Stevens-Johnson syndrome. Patients with a history of anaphylactoid reactions to codeine and other opioids may be at increased risk and therefore should not receive tramadol hydrochloride extended-release tablets (see CONTRAINDICATIONS).
  Respiratory Depression
  Administer tramadol hydrochloride extended-release tablets cautiously in patients at risk for respiratory depression. In these patients alternative non-opioid analgesics should be considered. When large doses of tramadol are administered with anesthetic medications or alcohol, respiratory depression may result. Respiratory depression should be treated as an overdose. If naloxone is to be administered, use cautiously because it may precipitate seizures (see WARNINGS Seizure Risk and OVERDOSAGE).
  Interaction With Central Nervous System (CNS) Depressants
  Tramadol hydrochloride extended-release tablets should be used with caution and in reduced dosages when administered to patients receiving CNS depressants such as alcohol, opioids, anesthetic agents, narcotics, phenothiazines, tranquilizers or sedative hypnotics. Tramadol hydrochloride extended-release tablets increase the risk of CNS and respiratory depression in these patients.
  Increased Intracranial Pressure or Head Trauma
  Tramadol hydrochloride extended-release tablets should be used with caution in patients with increased intracranial pressure or head injury. The respiratory depressant effects of opioids include carbon dioxide retention and secondary elevation of cerebrospinal fluid pressure, and may be markedly exaggerated in these patients. Additionally, pupillary changes (miosis) from tramadol may obscure the existence, extent, or course of intracranial pathology. Clinicians should also maintain a high index of suspicion for adverse drug reaction when evaluating altered mental status in these patients if they are receiving tramadol hydrochloride extended-release tablets. (see WARNINGS - Respiratory Depression).
  Use in Ambulatory Patients
  Tramadol hydrochloride extended-release tablets may impair the mental and or physical abilities required for the performance of potentially hazardous tasks such as driving a car or operating machinery. The patient using this drug should be cautioned accordingly.
  Use With MAO Inhibitors and Serotonin Re-uptake Inhibitors
  Use tramadol hydrochloride extended-release tablets with great caution in patients taking monoamine oxidase inhibitors. Animal studies have shown increased deaths with combined administration. Concomitant use of tramadol hydrochloride extended-release tablets with MAO inhibitors or SSRIs increases the risk of adverse events, including seizure and serotonin syndrome.
  Withdrawal
  Withdrawal symptoms may occur if tramadol hydrochloride extended-release tablet is discontinued abruptly. These symptoms may include: anxiety, sweating, insomnia, rigors, pain, nausea, tremors, diarrhea, upper respiratory symptoms, piloerection, and rarely hallucinations. Clinical experience suggests that withdrawal symptoms may be reduced by tapering tramadol hydrochloride extended-release tablets.
  Misuse, Abuse and Diversion of Opioids
  Tramadol is an opioid agonist of the morphine-type. Such drugs are sought by drug abusers and people with addiction disorders and are subject to criminal diversion.
  Tramadol can be abused in a manner similar to other opioid agonists, legal or illicit. This should be considered when prescribing or dispensing tramadol hydrochloride extended-release tablets in situations where the physician or pharmacist is concerned about an increased risk of misuse, abuse, or diversion.
  Tramadol hydrochloride extended-release tablets could be abused by crushing, chewing, snorting, or injecting the dissolved product. These practices will result in the uncontrolled delivery of the opioid and pose a significant risk to the abuser that could result in overdose and death (see WARNINGS and DRUG ABUSE AND ADDICTION).
  Concerns about abuse, addiction, and diversion should not prevent the proper management of pain. The development of addiction to opioid analgesics in properly managed patients with pain has been reported to be rare. However, data are not available to establish the true incidence of addiction in chronic pain patients.
  Healthcare professionals should contact their State Professional Licensing Board, or State Controlled Substances Authority for information on how to prevent and detect abuse or diversion of this product.
  Interactions with Alcohol and Drugs of Abuse
  Tramadol may be expected to have additive effects when used in conjunction with alcohol, other opioids, or illicit drugs that cause central nervous system depression.

DRUG ABUSE AND DEPENDENCE SECTION

- Tramadol hydrochloride extended-release tablet is a mu-agonist opioid. Tramadol, like other opioids used in analgesia, can be abused and is subject to criminal diversion.
  Drug addiction is characterized by compulsive use, use for non-medical purposes, and continued use despite harm or risk of harm. Drug addiction is a treatable disease, utilizing a multi-disciplinary approach, but relapse is common.
  “Drug-seeking” behavior is very common in addicts and drug abusers. Drug-seeking tactics include emergency calls or visits near the end of office hours, refusal to undergo appropriate examination, testing or referral, repeated “loss” of prescriptions, tampering with prescriptions and reluctance to provide prior medical records or contact information for other treating physician(s). “Doctor shopping” to obtain additional prescriptions is common among drug abusers and people suffering from untreated addiction.
  Abuse and addiction are separate and distinct from physical dependence and tolerance. Physicians should be aware that addiction may not be accompanied by concurrent tolerance and symptoms of physical dependence in all addicts. In addition, abuse of opioids can occur in the absence of true addiction and is characterized by misuse for non- medical purposes, often in combination with other psychoactive substances. Tramadol hydrochloride extended-release tablets, like other opioids, may be diverted for non-medical use. Careful record-keeping of prescribing information, including quantity, frequency, and renewal requests is strongly advised.
  Proper assessment of the patient, proper prescribing practices, periodic re-evaluation of therapy, and proper dispensing and storage are appropriate measures that help to limit abuse of opioid drugs.
  Tramadol hydrochloride extended-release tablets are intended for oral use only. The crushed tablet poses a hazard of overdose and death. This risk is increased with concurrent abuse of alcohol and other substances. With parenteral abuse, the tablet excipients can be expected to result in local tissue necrosis, infection, pulmonary granulomas, and increased risk of endocarditis and valvular heart injury. Parenteral drug abuse is commonly associated with transmission of infectious diseases such as hepatitis and HIV.
  Risk of Overdosage
  Serious potential consequences of overdosage with tramadol hydrochloride extended-release tablets are central nervous system depression, respiratory depression and death. In treating an overdose, primary attention should be given to maintaining adequate ventilation along with general supportive treatment (see OVERDOSAGE).

PRECAUTIONS SECTION

Acute Abdominal Condition

The administration of tramadol hydrochloride extended-release tablets may complicate the clinical assessment of patients with acute abdominal conditions.

Use in Renal and Hepatic Disease

Impaired renal function results in a decreased rate and extent of excretion of tramadol and its active metabolite, M1. Tramadol hydrochloride extended-release tablets have not been studied in patients with severe renal impairment (CLcr < 30 mL/min). The limited availability of dose strengths and once daily dosing of tramadol hydrochloride extended-release tablets do not permit the dosing flexibility required for safe use in patients with severe renal impairment. Therefore, tramadol hydrochloride extended-release tablets should not be used in patients with severe renal impairment (see CLINICAL PHARMACOLOGY and DOSAGE AND ADMINISTRATION).

Metabolism of tramadol and M1 is reduced in patients with advanced cirrhosis of the liver. The pharmacokinetics of tramadol hydrochloride extended-release tablets has not been studied in patients with severe hepatic impairment. The limited availability of dose strengths and once daily dosing of tramadol hydrochloride extended-release tablets do not permit the dosing flexibility required for safe use in patients with severe hepatic impairment. Therefore, tramadol hydrochloride extended-release tablets should not be used in patients with severe hepatic impairment (see CLINICAL PHARMACOLOGY and DOSAGE AND ADMINISTRATION).

INFORMATION FOR PATIENTS SECTION

-
  - Patients should be informed that tramadol hydrochloride extended-release tablets is for oral use only and should be swallowed whole. The tablets should not be chewed, crushed, or split.
  - Patients should be informed that tramadol hydrochloride extended-release tablets may cause seizures and/or serotonin syndrome with concomitant use of serotonergic agents (including SRIs, NRIs, and triptans) or drugs that significantly reduce the metabolic clearance of tramadol.
  - Patients should be informed that tramadol hydrochloride extended-release tablets may impair mental or physical abilities required for the performance of potentially hazardous tasks such as driving a car or operating machinery.
  - Patients should be informed that tramadol hydrochloride extended-release tablets should not be taken with alcohol containing beverages.
  - Patients should be informed that tramadol hydrochloride extended-release tablets should be used with caution when taking medications such as tranquilizers, hypnotics or other opiate containing analgesics.
  - Female patients should be instructed to inform the prescriber if they are pregnant, think they might become pregnant, or are trying to become pregnant (see PRECAUTIONS, Labor and Delivery).
  - Patients should be educated regarding the single-dose and 24-hour dosing regimen, as exceeding these recommendations can result in respiratory depression, seizures or death.
  Use in Drug and Alcohol Addiction
  Tramadol hydrochloride extended-release tablet is an opioid with no approved use in the management of addictive disorders. Its proper usage in individuals with drug or alcohol dependence, either active or in remission, is for the management of pain requiring opioid analgesia.
  Drug Interactions
  CYP2D6 and CYP3A4 inhibitors: Concomitant administration of CYP2D6 and/or CYP3A4 inhibitors (See CLINICAL PHARMACOLOGY - Pharmacokinetics), such as quinidine, fluoxetine, paroxetine and amitriptyline (CYP2D6 inhibitors), and ketoconazole and erythromycin (CYP3A4 inhibitors), may reduce metabolic clearance of tramadol increasing the risk for serious adverse events including seizures and serotonin syndrome.
  Serotonergic Drugs: There have been postmarketing reports of serotonin syndrome with use of tramadol and SSRIs/SNRIs or MAOIs and α2-adrenergic blockers. Caution is advised when tramadol hydrochloride extended-release tablets are coadministered with other drugs that may affect the serotonergic neurotransmitter systems, such as SSRIs, MAOIs, triptans, linezolid (an antibiotic which is a reversible non-selective MAOI), lithium, or St. John's Wort. If concomitant treatment of tramadol hydrochloride extended-release tablets with a drug affecting the serotonergic neurotransmitter system is clinically warranted, careful observation of the patient is advised, particularly during treatment initiation and dose increases (see WARNINGS - Serotonin Syndrome).
  Triptans: Based on the mechanism of action of tramadol and the potential for serotonin syndrome, caution is advised when tramadol hydrochloride extended-release tablets are coadministered with a triptan. If concomitant treatment of tramadol hydrochloride extended-release tablets with a triptan is clinically warranted, careful observation of the patient is advised, particularly during treatment initiation and dose increases (see WARNINGS - Serotonin Syndrome).
  Use With Carbamazepine
  Patients taking carbamazepine, a CYP3A4 inducer, may have a significantly reduced analgesic effect of tramadol. Because carbamazepine increases tramadol metabolism and because of the seizure risk associated with tramadol, concomitant administration of tramadol hydrochloride extended-release tablets and carbamazepine is not recommended.
  Use With Quinidine
  Coadministration of quinidine with tramadol hydrochloride extended-release tablets resulted in a 50% to 60% increase in tramadol exposure and a 50% to 60% decrease in M1 exposure (see CLINICAL PHARMACOLOGY, Drug Interactions). The clinical consequences of these findings are unknown.
  Use With Digoxin and Warfarin
  Postmarketing surveillance of tramadol has revealed rare reports of digoxin toxicity and alteration of warfarin effect, including elevation of prothrombin times.
  Potential for Other Drugs to Affect Tramadol
  In vitro drug interaction studies in human liver microsomes indicate that concomitant administration with inhibitors of CYP2D6 such as fluoxetine, paroxetine, and amitriptyline could result in some inhibition of the metabolism of tramadol. Administration of CYP3A4 inhibitors, such as ketoconazole and erythromycin, or inducers, such as rifampin and St. John’s Wort, with tramadol hydrochloride extended-release tablets may affect the metabolism of tramadol leading to altered tramadol exposure.
  Potential for Tramadol to Affect Other Drugs
  In vitro drug interaction studies in human liver microsomes indicate that tramadol has no effect on quinidine metabolism. In vitro studies indicate that tramadol is unlikely to inhibit the CYP3A4-mediated metabolism of other drugs when administered concomitantly at therapeutic doses. Tramadol is a mild inducer of selected drug metabolism pathways measured in animals.
  Carcinogenesis, Mutagenesis, Impairment of Fertility
  No carcinogenic effect of tramadol was observed in p53(+/–)-heterozygous mice at oral doses up to 150 mg/kg/day (approximately 2-fold maximum daily human dose [MDHD] of 400 mg/day for a 60 kg adult based on body surface conversion) for 26 weeks and in rats at oral doses up to 75 mg/kg/day for males and 100 mg/kg/day for females (approximately 2-fold MDHD) for two years. However, the excessive decrease in body weight gain observed in the rat study might have reduced their sensitivity to any potential carcinogenic effect of the drug.
  Tramadol was not mutagenic in the following assays: a bacterial reverse mutation assay using Salmonella and E. coli, a mouse lymphoma assay (in the absence of metabolic activation), and a bone marrow micronucleus test in mice. Mutagenic results occurred in the presence of metabolic activation in the mouse lymphoma assay. Overall, the weight of evidence from these tests indicates that tramadol does not pose a genotoxic risk to humans.
  No effects on fertility were observed for tramadol at oral dose levels up to 50 mg/kg/day in male and female rats (approximately equivalent to MDHD).
  Pregnancy
  Teratogenic Effects: Pregnancy Category C
  Tramadol was not teratogenic at oral dose levels up to 50 mg/kg/day (approximately equivalent to MDHD) in rats and 100 mg/kg (approximately 5-fold MDHD) in rabbits during organogenesis. However, embryo-fetal lethality, reductions in fetal weight and skeletal ossification, and increased supernumerary ribs were observed at a maternal toxic dose of 140 mg/kg in mice (approximately 2-fold MDHD), 80 mg/kg in rats (2-fold MDHD) or 300 mg/kg in rabbits (approximately 15-fold MDHD).
  Non-teratogenic Effects
  Tramadol caused a reduction in neonatal body weight and survival at an oral dose of 80 mg/kg (approximately 2-fold MDHD) when rats were treated during late gestation throughout lactation period.
  There are no adequate and well-controlled studies in pregnant women. Tramadol hydrochloride extended-release tablets should be used during pregnancy only if the potential benefit justifies the potential risk to the fetus. Neonatal seizures, neonatal withdrawal syndrome, fetal death and still birth have been reported during postmarketing reports with tramadol hydrochloride immediate-release products.
  Labor and Delivery
  Tramadol hydrochloride extended-release tablets should not be used in pregnant women prior to or during labor unless the potential benefits outweigh the risks. Safe use in pregnancy has not been established. Chronic use during pregnancy may lead to physical dependence and post-partum withdrawal symptoms in the newborn (see DRUG ABUSE AND ADDICTION). Tramadol has been shown to cross the placenta. The mean ratio of serum tramadol in the umbilical veins compared to maternal veins was 0.83 for 40 women treated with tramadol hydrochloride during labor.
  The effect of tramadol hydrochloride extended-release tablets, if any, on the later growth, development, and functional maturation of the child is unknown.
  Nursing Mothers
  Tramadol hydrochloride extended-release tablets are not recommended for obstetrical preoperative medication or for post-delivery analgesia in nursing mothers because its safety in infants and newborns has not been studied. Following a single intravenous 100 mg dose of tramadol, the cumulative excretion in breast milk within sixteen hours postdose was 100 mcg of tramadol (0.1% of the maternal dose) and 27 mcg of M1.
  Pediatric Use
  The safety and efficacy of tramadol hydrochloride extended-release tablets in patients under 18 years of age have not been established. The use of tramadol hydrochloride extended-release tablets in the pediatric population is not recommended.
  Geriatric Use
  Nine-hundred-one elderly (65 years of age or older) subjects were exposed to tramadol hydrochloride extended-release tablets in clinical trials. Of those subjects, 156 were 75 years of age and older. In general, higher incidence rates of adverse events were observed for patients older than 65 years of age compared with patients 65 years and younger, particularly for the following adverse events: constipation, fatigue, weakness, postural hypotension and dyspepsia. For this reason, tramadol hydrochloride extended-release tablets should be used with great caution in patients older than 75 years of age (see CLINICAL PHARMACOLOGY and DOSAGE AND ADMINISTRATION).

ADVERSE REACTIONS SECTION

The following serious adverse reactions are described, or described in greater detail, in other sections:

Addiction, Abuse, and Misuse [see WARNINGS AND PRECAUTIONS (5.1)]
Life-Threatening Respiratory Depression [see WARNINGS AND PRECAUTIONS (5.3)]
Ultra-Rapid Metabolism of Tramadol and Other Risk Factors for Life-threatening Respiratory Depression in Children [see WARNINGS AND PRECAUTIONS (5.4)]
Neonatal Opioid Withdrawal Syndrome [see WARNINGS AND PRECAUTIONS (5.5)]
Interactions with Benzodiazepines or Other CNS Depressants [see WARNINGS AND PRECAUTIONS (5.7)]
Serotonin Syndrome [see WARNINGS AND PRECAUTIONS (5.8)]
Seizures [see WARNINGS AND PRECAUTIONS (5.9)]
Suicide [see WARNINGS AND PRECAUTIONS (5.10)]
Adrenal Insufficiency [see WARNINGS AND PRECAUTIONS (5.11)]
Severe Hypotension [see WARNINGS AND PRECAUTIONS (5.13)]
Gastrointestinal Adverse Reactions [see WARNINGS AND PRECAUTIONS (5.15)]
Hypersensitivity Reactions [see WARNINGS AND PRECAUTIONS (5.16)]
Withdrawal [see WARNINGS AND PRECAUTIONS (5.17)]

6.1 Clinical Trials Experience

Because clinical trials are conducted under widely varying conditions, adverse reaction rates observed in the clinical trials of a drug cannot be directly compared to rates in the clinical trials of another drug and may not reflect the rates observed in practice.

Tramadol hydrochloride was administered to 550 patients during the double-blind or open-label extension periods in U.S. studies of chronic nonmalignant pain. Of these patients, 375 were 65 years old or older. Table 1 reports the cumulative incidence rate of adverse reactions by 7, 30 and 90 days for the most frequent reactions (5% or more by 7 days). The most frequently reported events were in the central nervous system and gastrointestinal system. Although the reactions listed in the table are felt to be probably related to tramadol hydrochloride administration, the reported rates also include some events that may have been due to underlying disease or concomitant medication. The overall incidence rates of adverse experiences in these trials were similar for tramadol hydrochloride and the active control groups, TYLENOL with Codeine #3 (acetaminophen 300 mg with codeine phosphate 30 mg), and aspirin 325 mg with codeine phosphate 30 mg, however, the rates of withdrawals due to adverse events appeared to be higher in the tramadol hydrochloride groups.

Table 1: Cumulative Incidence of Adverse Reactions for Tramadol Hydrochloride in Chronic Trials of Nonmalignant Pain (N=427)

Up to 7 Days

Up to 30 Days

Up to 90 Days

Dizziness/Vertigo

26%

31%

33%

Nausea

24%

34%

40%

Constipation

24%

38%

46%

Headache

18%

26%

32%

Somnolence

16%

23%

25%

Vomiting

9%

13%

17%

Pruritus

8%

10%

11%

“CNS Stimulation”1

7%

11%

14%

Asthenia

6%

11%

12%

Sweating

6%

7%

9%

Dyspepsia

5%

9%

13%

Dry Mouth

5%

9%

10%

Diarrhea

5%

6%

10%

1 “CNS Stimulation” is a composite of nervousness, anxiety, agitation, tremor, spasticity, euphoria, emotional lability and hallucinations

Incidence 1% to Less than 5% Possibly Causally Related

The following lists adverse reactions that occurred with an incidence of 1% to less than 5% in clinical trials, and for which the possibility of a causal relationship with tramadol hydrochloride exists.

Body as a Whole: Malaise.

Cardiovascular: Vasodilation.

Central Nervous System: Anxiety, Confusion, Coordination disturbance, Euphoria, Miosis, Nervousness, Sleep disorder.

Gastrointestinal: Abdominal pain, Anorexia, Flatulence.

Musculoskeletal: Hypertonia.

Skin: Rash.

Special Senses: Visual disturbance.

Urogenital: Menopausal symptoms, Urinary frequency, Urinary retention.

Incidence Less than 1%, Possibly Causally Related

The following lists adverse reactions that occurred with an incidence of less than 1% in clinical trials of tramadol and/or reported in postmarketing experience with tramadol-containing products.

Body as a Whole: Accidental injury, Allergic reaction, Anaphylaxis, Death, Suicidal tendency, Weight loss, Serotonin syndrome (mental status change, hyperreflexia, fever, shivering, tremor, agitation, diaphoresis, seizures and coma).

Cardiovascular: Orthostatic hypotension, Syncope, Tachycardia.

Central Nervous System: Abnormal gait, Amnesia, Cognitive dysfunction, Depression, Difficulty in concentration, Hallucinations, Paresthesia, Seizure, Tremor.

Respiratory: Dyspnea.

Skin: Stevens-Johnson syndrome/Toxic epidermal necrolysis, Urticaria, Vesicles.

Special Senses: Dysgeusia.

Urogenital: Dysuria, Menstrual disorder.

Other Adverse Experiences, Causal Relationship Unknown

A variety of other adverse events were reported infrequently in patients taking tramadol hydrochloride during clinical trials and/or reported in postmarketing experience. A causal relationship between tramadol hydrochloride and these events has not been determined. However, the most significant events are listed below as alerting information to the physician.

Cardiovascular: Abnormal ECG, Hypertension, Hypotension, Myocardial ischemia, Palpitations, Pulmonary edema, Pulmonary embolism.

Central Nervous System: Migraine.

Gastrointestinal: Gastrointestinal bleeding, Hepatitis, Stomatitis, Liver failure.

Laboratory Abnormalities: Creatinine increase, Elevated liver enzymes, Hemoglobin decrease, Proteinuria.

Sensory: Cataracts, Deafness, Tinnitus.

6.2 Post-marketing Experience

The following adverse reactions have been identified during post-approval use of tramadol hydrochloride. Because these reactions are reported voluntarily from a population of uncertain size, it is not always possible to reliably estimate their frequency or establish a causal relationship to drug exposure.

Serotonin syndrome: Cases of serotonin syndrome, a potentially life-threatening condition, have been reported during concomitant use of opioids with serotonergic drugs.

Adrenal insufficiency: Cases of adrenal insufficiency have been reported with opioid use, more often following greater than one month of use.

Androgen deficiency: Cases of androgen deficiency have occurred with chronic use of opioids [see CLINICAL PHARMACOLOGY (12.2)].

QT prolongation/torsade de pointes: Cases of QT prolongation and/or torsade de pointes have been reported with tramadol use. Many of these cases were reported in patients taking another drug labeled for QT prolongation, in patients with a risk factor for QT prolongation (e.g., hypokalemia), or in the overdose setting.

Eye disorders – mydriasis

Metabolism and nutrition disorders – Hyponatremia: Cases of severe hyponatremia and/or SIADH have been reported in patients taking tramadol, most often in females over the age of 65, and within the first week of therapy [see WARNINGS AND PRECAUTIONS (5.19)].
Hypoglycemia: Cases of hypoglycemia have been reported in patients taking tramadol. Most reports were in patients with predisposing risk factors, including diabetes or renal insufficiency, or in elderly patients [see WARNINGS AND PRECAUTIONS (5.20)].

Nervous system disorders – movement disorder, speech disorder

Psychiatric disorders – delirium

OVERDOSAGE SECTION

Acute overdosage with tramadol can be manifested by respiratory depression, somnolence progressing to stupor or coma, skeletal muscle flaccidity, cold and clammy skin, constricted pupils, bradycardia, hypotension, and death.

Deaths due to overdose have been reported with abuse and misuse of tramadol, by ingesting, inhaling, or injecting the crushed tablets. Review of case reports has indicated that the risk of fatal overdose is further increased when tramadol is abused concurrently with alcohol or other CNS depressants, including other opioids.

In the treatment of tramadol overdosage, primary attention should be given to the re- establishment of a patent airway and institution of assisted or controlled ventilation. Supportive measures (including oxygen and vasopressors) should be employed in the management of circulatory shock and pulmonary edema accompanying overdose as indicated. Cardiac arrest or arrhythmias may require cardiac massage or defibrillation.

While naloxone will reverse some, but not all, symptoms caused by overdosage with tramadol, the risk of seizures is also increased with naloxone administration. In animals convulsions following the administration of toxic doses of tramadol could be suppressed with barbiturates or benzodiazepines but were increased with naloxone. Naloxone administration did not change the lethality of an overdose in mice. Hemodialysis is not expected to be helpful in an overdose because it removes less than 7% of the administered dose in a 4-hour dialysis period.

DOSAGE & ADMINISTRATION SECTION

Tramadol hydrochloride extended-release tablets should not be used in patients with:
creatinine clearance less than 30 mL/min,
severe hepatic impairment (Child-Pugh Class C)

(See PRECAUTIONS, Use in Renal and Hepatic Disease).

Tramadol hydrochloride extended-release tablets must be swallowed whole and must not be chewed, crushed, or split (see WARNINGS, Misuse, Abuse and Diversion of Opioids and DRUG ABUSE AND ADDICTION).

Adults (18 years of age and over)

Patients Not Currently on Tramadol Immediate-Release Products

For patients not currently treated with tramadol immediate-release (IR) products, tramadol hydrochloride extended-release tablets should be initiated at a dose of 100 mg once daily and titrated up as necessary by 100 mg increments every five days to relief of pain and depending upon tolerability. Tramadol hydrochloride extended-release tablets should not be administered at a dose exceeding 300 mg per day.

Patients Currently on Tramadol Immediate-Release Products

For patients maintained on tramadol IR products, calculate the 24-hour tramadol immediate-release (IR) dose and initiate a total daily dose of tramadol hydrochloride extended-release tablets rounded down to the next lowest 100 mg increment. The dose may subsequently be individualized according to patient need. Due to limitations in flexibility of dose selection with tramadol hydrochloride extended-release tablets, some patients maintained on tramadol IR products may not be able to convert to tramadol hydrochloride extended-release tablets. Tramadol hydrochloride extended-release tablets should not be administered at a dose exceeding 300 mg per day. The concomitant use of tramadol hydrochloride extended-release tablets with other tramadol products is not recommended (see WARNINGS).

Individualization of Dose

Good pain management practice dictates that the dose be individualized according to patient need using the lowest beneficial dose. Start at the lowest possible dose and titrate upward as tolerated to achieve an adequate effect. Clinical studies of tramadol hydrochloride extended-release tablets have not demonstrated a clinical benefit at a total daily dose exceeding 300 mg.

In general, dosing of an elderly patient (over 65 years of age) should be initiated cautiously, usually starting at the low end of the dosing range, reflecting the greater frequency of decreased hepatic, renal or cardiac function and of concomitant disease or other drug therapy. Tramadol hydrochloride extended-release tablets should be administered with even greater caution in patients over 75 years, due to the greater frequency of adverse events seen in this population.

HOW SUPPLIED SECTION

Tramadol hydrochloride extended-release tablets USP are supplied in the following package and dose strength forms:

100 mg tablets (white to off-white circular, biconvex, beveled edge, coated) imprinted with 'L010' on one side and plain on the other side.

Bottles of 30 tablets: NDC 68180-697-06

Bottles of 100 tablets: NDC 68180-697-01

Bottles of 500 tablets: NDC 68180-697-02

200 mg tablets (white to off-white circular, biconvex, beveled edge, coated) imprinted with 'L011' on one side and plain on the other side.

Bottles of 30 tablets: NDC 68180-698-06

Bottles of 100 tablets: NDC 68180-698-01

Bottles of 500 tablets: NDC 68180-698-02

300 mg tablets (white to off-white circular, biconvex, beveled edge, coated) imprinted with 'L012' on one side and plain on the other side

Bottles of 30 tablets: NDC 68180-699-06

Bottles of 100 tablets: NDC 68180-699-01

BOXED WARNING

WARNING: ADDICTION, ABUSE, AND MISUSE; RISK EVALUATION AND MITIGATION STRATEGY (REMS); LIFE-THREATENING RESPIRATORY DEPRESSION; ACCIDENTAL INGESTION; ULTRA-RAPID METABOLISM OF TRAMADOL AND OTHER RISK FACTORS FOR LIFE-THREATENING RESPIRATORY DEPRESSION IN CHILDREN; NEONATAL OPIOID WITHDRAWAL SYNDROME; INTERACTIONS WITH DRUGS AFFECTING CYTOCHROME P450 ISOENZYMES; and RISKS FROM CONCOMITANT USE WITH BENZODIAZEPINES OR OTHER CNS DEPRESSANTS

Addiction, Abuse, and Misuse

Tramadol hydrochloride extended-release tablet exposes patients and other users to the risks of opioid addiction, abuse, and misuse, which can lead to overdose and death. Assess each patient's risk prior to prescribing tramadol hydrochloride extended-release tablets, and monitor all patients regularly for the development of these behaviors and conditions [see Warnings and Precautions (5.1)].

Opioid Analgesic Risk Evaluation and Mitigation Strategy (REMS)

To ensure that the benefits of opioid analgesics outweigh the risks of addiction, abuse, and misuse, the Food and Drug Administration (FDA) has required a REMS for these products [see Warnings and Precautions (5.2)]. Under the requirements of the REMS, drug companies with approved opioid analgesic products must make REMS-compliant education programs available to healthcare providers. Healthcare providers are strongly encouraged to

• complete a REMS-compliant education program,

• counsel patients and/or their caregivers, with every prescription, on safe use, serious risks, storage, and disposal of these products,

• emphasize to patients and their caregivers the importance of reading the Medication Guide every time it is provided by their pharmacist, and

• consider other tools to improve patient, household, and community safety.

Life-Threatening Respiratory Depression

Serious, life-threatening, or fatal respiratory depression may occur with use of tramadol hydrochloride extended-release tablets. Monitor for respiratory depression, especially during initiation of tramadol hydrochloride extended-release tablets or following a dose increase. Instruct patients to swallow tramadol hydrochloride extended-release tablets intact, and not to cut, break, chew, crush, or dissolve the tablets to avoid exposure to a potentially fatal dose of tramadol [see Warnings and Precautions (5.3)].

Accidental Ingestion

Accidental ingestion of even one dose of tramadol hydrochloride extended-release tablets, especially by children, can result in a fatal overdose of tramadol [see Warnings and Precautions (5.3)].

Ultra-Rapid Metabolism Of Tramadol And Other Risk Factors For Life-Threatening Respiratory Depression In Children

Life-threatening respiratory depression and death have occurred in children who received tramadol. Some of the reported cases followed tonsillectomy and/or adenoidectomy; in at least one case, the child had evidence of being an ultra-rapid metabolizer of tramadol due to a CYP2D6 polymorphism [see Warnings and Precautions (5.4)]. Tramadol hydrochloride extended-release tablets are contraindicated in children younger than 12 years of age and in children younger than 18 years of age following tonsillectomy and/or adenoidectomy [see Contraindications (4)]. Avoid the use of tramadol hydrochloride extended-release tablets in adolescents 12 to 18 years of age who have other risk factors that may increase their sensitivity to the respiratory depressant effects of tramadol. [see Warnings and Precautions (5.4)]

Neonatal Opioid Withdrawal Syndrome

Prolonged use of tramadol hydrochloride extended-release tablets during pregnancy can result in neonatal opioid withdrawal syndrome, which may be life-threatening if not recognized and treated, and requires management according to protocols developed by neonatology experts. If opioid use is required for a prolonged period in a pregnant woman, advise the patient of the risk of neonatal opioid withdrawal syndrome and ensure that appropriate treatment will be available [see Warnings and Precautions (5.5)].

Interactions with Drugs Affecting Cytochrome P450 Isoenzymes

The effects of concomitant use or discontinuation of cytochrome P450 3A4 inducers, 3A4 inhibitors, or 2D6 inhibitors with tramadol are complex. Use of cytochrome P450 3A4 inducers, 3A4 inhibitors, or 2D6 inhibitors with tramadol hydrochloride extended-release tablet requires careful consideration of the effects on the parent drug, tramadol, and the active metabolite, M1 [see Warnings and Precautions (5.6), Drug Interactions (7)].

Risks From Concomitant Use With Benzodiazepines Or Other CNS Depressants Concomitant use of opioids with benzodiazepines or other central nervous system (CNS) depressants, including alcohol, may result in profound sedation, respiratory depression, coma, and death [see Warnings and Precautions (5.7), Drug Interactions (7)].

Reserve concomitant prescribing of tramadol hydrochloride extended-release Injection and benzodiazepines or other CNS depressants for use in patients for whom alternative treatment options are inadequate.
Limit dosages and durations to the minimum required.
Follow patients for signs and symptoms of respiratory depression and sedation.

DOSAGE FORMS AND STRENGTHS

Extended-release tablets are available as:

100 mg tablets: White to off-white circular, biconvex, beveled edge coated tablets imprinted with 'L010' on one side and plain on the other side.

200 mg tablets: White to off-white circular, biconvex, beveled edge coated tablets imprinted with 'L011' on one side and plain on the other side.

300 mg tablets: White to off-white circular, biconvex, beveled edge coated tablets imprinted with 'L012' on one side and plain on the other side.

DRUG INTERACTIONS

Table 2 includes clinically significant drug interactions with tramadol hydrochloride extended-release tablets.

Inhibitors of CYP2D6
Clinical Impact:
The concomitant use of tramadol hydrochloride extended-release tablets and CYP2D6 inhibitors may result in an increase in the plasma concentration of tramadol and a decrease in the plasma concentration of M1, particularly when an inhibitor is added after a stable dose of tramadol hydrochloride extended-release tablets is achieved. Since M1 is a more potent µ-opioid agonist, decreased M1 exposure could result in decreased therapeutic effects, and may result in signs and symptoms of opioid withdrawal in patients who had developed physical dependence to tramadol. Increased tramadol exposure can result in increased or prolonged therapeutic effects and increased risk for serious adverse events including seizures and serotonin syndrome.
After stopping a CYP2D6 inhibitor, as the effects of the inhibitor decline, the tramadol plasma concentration will decrease and the M1 plasma concentration will increase which could increase or prolong therapeutic effects but also increase adverse reactions related to opioid toxicity, and may cause potentially fatal respiratory depression [see Clinical Pharmacology (12.3)] .
Intervention:
If concomitant use of a CYP2D6 inhibitor is necessary, follow patients closely for adverse reactions including opioid withdrawal, seizures, and serotonin syndrome.
If a CYP2D6 inhibitor is discontinued, consider lowering tramadol hydrochloride extended-release tablets dosage until stable drug effects are achieved. Follow patients closely for adverse events including respiratory depression and sedation.
Examples
Quinidine, fluoxetine, paroxetine and bupropion
Inhibitors of CYP3A4
Clinical Impact:
The concomitant use of tramadol hydrochloride extended-release tablets and CYP3A4 inhibitors can increase the plasma concentration of tramadol and may result in a greater amount of metabolism via CYP2D6 and greater levels of M1. Follow patients closely for increased risk of serious adverse events including seizures and serotonin syndrome, and adverse reactions related to opioid toxicity including potentially fatal respiratory depression, particularly when an inhibitor is added after a stable dose of tramadol hydrochloride extended-release tablets is achieved.
After stopping a CYP3A4 inhibitor, as the effects of the inhibitor decline, the tramadol plasma concentration will decrease [see Clinical Pharmacology (12.3)] , resulting in decreased opioid efficacy and possibly signs and symptoms of opioid withdrawal in patients who had developed physical dependence to tramadol.
Intervention:
If concomitant use is necessary, consider dosage reduction of tramadol hydrochloride extended-release tablets until stable drug effects are achieved. Follow patients closely for seizures and serotonin syndrome, and signs of respiratory depression and sedation at frequent intervals.
If a CYP3A4 inhibitor is discontinued, consider increasing the tramadol hydrochloride extended-release tablets dosage until stable drug effects are achieved and follow patients for signs and symptoms of opioid withdrawal.
Examples
Macrolide antibiotics (e.g., erythromycin), azole-antifungal agents (e.g. ketoconazole), protease inhibitors (e.g., ritonavir)
CYP3A4 Inducers
Clinical Impact:
The concomitant use of tramadol hydrochloride extended-release tablets and CYP3A4 inducers can decrease the plasma concentration of tramadol [see Clinical Pharmacology (12.3)] , resulting in decreased efficacy or onset of a withdrawal syndrome in patients who have developed physical dependence to tramadol, [see Warnings and Precautions (5.6)] .
After stopping a CYP3A4 inducer, as the effects of the inducer decline, the tramadol plasma concentration will increase [see Clinical Pharmacology (12.3)] , which could increase or prolong both the therapeutic effects and adverse reactions, and may cause seizures and serotonin syndrome, and potentially fatal respiratory depression.
Intervention:
If concomitant use is necessary, consider increasing the tramadol hydrochloride extended-release tablets dosage until stable drug effects are achieved. Follow patients for signs of opioid withdrawal.
If a CYP3A4 inducer is discontinued, consider tramadol hydrochloride extended-release tablets dosage reduction and monitor for seizures and serotonin syndrome, and signs of sedation and respiratory depression.
Patients taking carbamazepine, a CYP3A4 inducer, may have a significantly reduced analgesic effect of tramadol. Because carbamazepine increases tramadol metabolism and because of the seizure risk associated with tramadol, concomitant administration of tramadol hydrochloride extended-release tablets and carbamazepine is not recommended.
Examples:
Rifampin, carbamazepine, phenytoin
Benzodiazepines and Other Central Nervous System (CNS) Depressants
Clinical Impact:
Due to additive pharmacologic effect, the concomitant use of benzodiazepines or other CNS depressants, including alcohol, can increase the risk of hypotension, respiratory depression, profound sedation, coma, and death.
Intervention:
Reserve concomitant prescribing of these drugs for use in patients for whom alternative treatment options are inadequate. Limit dosages and durations to the minimum required. Follow patients closely for signs of respiratory depression and sedation [see Warnings and Precautions (5.7)] .
Examples:
Benzodiazepines and other sedatives/hypnotics, anxiolytics, tranquilizers, muscle relaxants, general anesthetics, antipsychotics, other opioids, alcohol.
Serotonergic Drugs
Clinical Impact:
The concomitant use of opioids with other drugs that affect the serotonergic neurotransmitter system has resulted in serotonin syndrome.
Intervention:
If concomitant use is warranted, carefully observe the patient, particularly during treatment initiation and dose adjustment. Discontinue tramadol hydrochloride extended-release tablets if serotonin syndrome is suspected.
Examples:
Selective serotonin reuptake inhibitors (SSRIs), serotonin and norepinephrine reuptake inhibitors (SNRIs), tricyclic antidepressants (TCAs), triptans, 5-HT3 receptor antagonists, drugs that affect the serotonin neurotransmitter system (e.g., mirtazapine, trazodone, tramadol), certain muscle relaxants (i.e., cyclobenzaprine, metaxalone), monoamine oxidase (MAO) inhibitors (those intended to treat psychiatric disorders and also others, such as linezolid and intravenous methylene blue).
Monoamine Oxidase Inhibitors (MAOIs)
Clinical Impact:
MAOI interactions with opioids may manifest as serotonin syndrome [see Warnings and Precautions (5.7)] or opioid toxicity (e.g., respiratory depression, coma) [see Warnings and Precautions (5.3)] .
Intervention:
Do not use tramadol hydrochloride extended-release tablets in patients taking MAOIs or within 14 days of stopping such treatment.
Examples:
phenelzine, tranylcypromine, linezolid
Mixed Agonist/Antagonist and Partial Agonist Opioid Analgesics
Clinical Impact:
May reduce the analgesic effect of tramadol hydrochloride extended-release tablets and/or precipitate withdrawal symptoms.
Intervention:
Avoid concomitant use.
Examples:
butorphanol, nalbuphine, pentazocine, buprenorphine
Muscle Relaxants
Clinical Impact:
Tramadol may enhance the neuromuscular blocking action of skeletal muscle relaxants and produce an increased degree of respiratory depression.
Intervention:
Monitor patients for signs of respiratory depression that may be greater than otherwise expected and decrease the dosage of tramadol hydrochloride extended-release tablets and/or the muscle relaxant as necessary.
Diuretics
Clinical Impact:
Opioids can reduce the efficacy of diuretics by inducing the release of antidiuretic hormone.
Intervention:
Monitor patients for signs of diminished diuresis and/or effects on blood pressure and increase the dosage of the diuretic as needed.
Anticholinergic Drugs
Clinical Impact:
The concomitant use of anticholinergic drugs may increase risk of urinary retention and/or severe constipation, which may lead to paralytic ileus.
Intervention:
Monitor patients for signs of urinary retention or reduced gastric motility when tramadol hydrochloride extended-release tablets are used concomitantly with anticholinergic drugs.
Digoxin
Clinical Impact:
Post-marketing surveillance of tramadol has revealed rare reports of digoxin toxicity.
Intervention:
Follow patients for signs of digoxin toxicity and adjust the dosage of digoxin as needed.
Warfarin
Clinical Impact:
Post-marketing surveillance of tramadol has revealed rare reports of alteration of warfarin effect, including elevation of prothrombin times.
Intervention:
Monitor the prothrombin time of patients on warfarin for signs of an interaction and adjust the dosage of warfarin as needed.

USE IN SPECIFIC POPULATIONS

8.1 Pregnancy

Risk Summary

Prolonged use of opioid analgesics during pregnancy may cause neonatal opioid withdrawal syndrome [see Warnings and Precautions (5.5)]. Available data with tramadol hydrochloride extended-release tablets in pregnant women are insufficient to inform a drug-associated risk for major birth defects and miscarriage.

In animal reproduction studies, tramadol administration during organogenesis decreased fetal weights and reduced ossification in mice, rats, and rabbits at 1.4, 0.6, and 3.6 times the maximum recommended human daily dosage (MRHD). Tramadol decreased pup body weight and increased pup mortality at 1.2 and 1.9 times the MRHD [see Data]. Based on animal data, advise pregnant women of the potential risk to a fetus.

The estimated background risk of major birth defects and miscarriage for the indicated population is unknown. All pregnancies have a background risk of birth defect, loss, or other adverse outcomes. In the U.S. general population, the estimated background risk of major birth defects and miscarriage in clinically recognized pregnancies is 2 to 4% and 15 to 20%, respectively.

Clinical Considerations

Fetal/Neonatal Adverse Reactions

Prolonged use of opioid analgesics during pregnancy for medical or nonmedical purposes can result in physical dependence in the neonate and neonatal opioid withdrawal syndrome shortly after birth. Neonatal opioid withdrawal syndrome presents as irritability, hyperactivity and abnormal sleep pattern, high pitched cry, tremor, vomiting, diarrhea, and failure to gain weight. The onset, duration, and severity of neonatal opioid withdrawal syndrome vary based on the specific opioid used, duration of use, timing and amount of last maternal use, and rate of elimination of the drug by the newborn. Observe newborns for symptoms and signs of neonatal opioid withdrawal syndrome and manage accordingly [see Warnings and Precautions (5.5)].

Neonatal seizures, neonatal withdrawal syndrome, fetal death and stillbirth have been reported with tramadol during post-approval use of tramadol immediate-release products.

Labor or Delivery

Opioids cross the placenta and may produce respiratory depression and psycho-physiologic effects in neonates. An opioid antagonist, such as naloxone, must be available for reversal of opioid-induced respiratory depression in the neonate. Tramadol hydrochloride extended-release tablets are not recommended for use in pregnant women during or immediately prior to labor, when use of shorter-acting analgesics or other analgesic techniques are more appropriate. Opioid analgesics, including tramadol hydrochloride extended-release tablets, can prolong labor through actions which temporarily reduce the strength, duration, and frequency of uterine contractions. However, this effect is not consistent and may be offset by an increased rate of cervical dilation, which tends to shorten labor. Monitor neonates exposed to opioid analgesics during labor for signs of excess sedation and respiratory depression.

Tramadol has been shown to cross the placenta. The mean ratio of serum tramadol in the umbilical veins compared to maternal veins was 0.83 for 40 women given tramadol during labor.

The effect of tramadol hydrochloride extended-release tablets, if any, on the later growth, development, and functional maturation of the child is unknown.

Data

Animal Data

Tramadol has been shown to be embryotoxic and fetotoxic in mice, (120 mg/kg), rats (25 mg/kg) and rabbits (75 mg/kg) at maternally toxic dosages, but was not teratogenic at these dose levels. These doses on a mg/m2 basis are 1.9, 0.8, and 4.9 times the maximum recommended human daily dosage (MRHD) for mouse, rat and rabbit, respectively.

No drug-related teratogenic effects were observed in progeny of mice (up to 140 mg/kg), rats (up to 80 mg/kg) or rabbits (up to 300 mg/kg) treated with tramadol by various routes. Embryo and fetal toxicity consisted primarily of decreased fetal weights, decreased skeletal ossification, and increased supernumerary ribs at maternally toxic dose levels. Transient delays in developmental or behavioral parameters were also seen in pups from rat dams allowed to deliver. Embryo and fetal lethality were reported only in one rabbit study at 300 mg/kg, a dose that would cause extreme maternal toxicity in the rabbit. The dosages listed for mouse, rat, and rabbit are 2.3, 2.6, and 19 times the MRHD, respectively.

Tramadol was evaluated in pre- and post-natal studies in rats. Progeny of dams receiving oral (gavage) dose levels of 50 mg/kg (1.6 times the MRHD) or greater had decreased weights, and pup survival was decreased early in lactation at 80 mg/kg (2.6 times the MRHD).

8.2 Lactation

Risk Summary

Tramadol hydrochloride extended-release tablets are not recommended for obstetrical preoperative medication or for post-delivery analgesia in nursing mothers because its safety in infants and newborns has not been studied.

Tramadol and its metabolite, O-desmethyl tramadol (M1), are present in human milk. There is no information on the effects of the drug on the breastfed infant or the effects of the drug on milk production. The M1 metabolite is more potent than tramadol in mu opioid receptor binding [see Clinical Pharmacology (12.1)]. Published studies have reported tramadol and M1 in colostrum with administration of tramadol to nursing mothers in the early post-partum period. Women who are ultra-rapid metabolizers of tramadol may have higher than expected serum levels of M1, potentially leading to higher levels of M1 in breast milk that can be dangerous in their breastfed infants. In women with normal tramadol metabolism, the amount of tramadol secreted into human milk is low and dose-dependent. Because of the potential for serious adverse reactions, including excess sedation and respiratory depression in a breastfed infant, advise patients that breastfeeding is not recommended during treatment with tramadol hydrochloride extended-release tablets.

Clinical Considerations

If infants are exposed to tramadol hydrochloride through breast milk, they should be monitored for excess sedation and respiratory depression. Withdrawal symptoms can occur in breastfed infants when maternal administration of an opioid analgesic is stopped, or when breast-feeding is stopped.

Data

Following a single IV 100 mg dose of tramadol, the cumulative excretion in breast milk within 16 hours post dose was 100 mcg of tramadol (0.1% of the maternal dose) and 27 mcg of M1.

8.3 Females and Males of Reproductive Potential

Infertility

Chronic use of opioids may cause reduced fertility in females and males of reproductive potential. It is not known whether these effects on fertility are reversible [see Adverse Reactions (6.2), Clinical Pharmacology (12.2), Nonclinical Toxicology (13.1)].

8.4 Pediatric Use

The safety and effectiveness of tramadol hydrochloride extended-release tablets in pediatric patients have not been established.

Life-threatening respiratory depression and death have occurred in children who received tramadol [see Warnings and Precautions (5.4)]. In some of the reported cases, these events followed tonsillectomy and/or adenoidectomy, and one of the children had evidence of being an ultra-rapid metabolizer of tramadol (i.e., multiple copies of the gene for cytochrome P450 isoenzyme 2D6). Children with sleep apnea may be particularly sensitive to the respiratory depressant effects of tramadol. Because of the risk of life-threatening respiratory depression and death:

Tramadol hydrochloride extended-release tablets are contraindicated for all children younger than 12 years of age [see Contraindications (4)] .
Tramadol hydrochloride extended-release tablets are contraindicated for post-operative management in pediatric patients younger than 18 years of age following tonsillectomy and/or adenoidectomy [see Contraindications (4)].
Avoid the use of tramadol hydrochloride extended-release tablets in adolescents 12 to 18 years of age who have other risk factors that may increase their sensitivity to the respiratory depressant effects of tramadol unless the benefits outweigh the risks. Risk factors include conditions associated with hypoventilation, such as postoperative status, obstructive sleep apnea, obesity, severe pulmonary disease, neuromuscular disease, and concomitant use of other medications that cause respiratory depression. [see Warnings and Precautions (5.4)].

8.5 Geriatric Use

Nine-hundred-one elderly (65 years of age or older) subjects were exposed to tramadol hydrochloride extended-release tablets in clinical trials. Of those subjects, 156 were 75 years of age and older. In general, higher incidence rates of adverse events were observed for patients older than 65 years of age compared with patients 65 years and younger, particularly for the following adverse events: constipation, fatigue, weakness, postural hypotension and dyspepsia. For this reason, tramadol hydrochloride extended-release tablets should be used with caution in patients over 65 years of age, and with even greater caution in patients older than 75 years of age [see Dosage and Administration (2.4), Clinical Pharmacology (12.3)].

Respiratory depression is the chief risk for elderly patients treated with opioids, and has occurred after large initial doses were administered to patients who were not opioid-tolerant or when opioids were co-administered with other agents that depress respiration. Titrate the dosage of tramadol hydrochloride extended-release tablets slowly in geriatric patients and monitor closely for signs of central nervous system and respiratory depression [see Warnings and Precautions (5.12)].

Tramadol is known to be substantially excreted by the kidney, and the risk of adverse reactions to this drug may be greater in patients with impaired renal function. Because elderly patients are more likely to have decreased renal function, care should be taken in dose selection, and it may be useful to monitor renal function.

8.6 Hepatic Impairment

Metabolism of tramadol and M1 is reduced in patients with advanced cirrhosis of the liver. Tramadol hydrochloride extended-release tablet has not been studied in patients with severe hepatic impairment. The limited availability of dose strengths and once daily dosing of tramadol hydrochloride extended-release tablets do not permit the dosing flexibility required for safe use in patients with severe hepatic impairment (Child-Pugh Class C). Therefore, tramadol hydrochloride extended-release tablets should not be used in patients with severe hepatic impairment [see Clinical Pharmacology (12.3)].

8.7 Renal Impairment

Impaired renal function results in a decreased rate and extent of excretion of tramadol and its active metabolite, M1. Tramadol hydrochloride extended-release tablet has not been studied in patients with severe renal impairment (CLcr < 30 mL/min). The limited availability of dose strengths and once daily dosing of tramadol hydrochloride extended-release tablets do not permit the dosing flexibility required for safe use in patients with severe renal impairment (Child-Pugh Class C). Therefore, tramadol hydrochloride extended-release tablets should not be used in patients with severe renal impairment [see Clinical Pharmacology (12.3)].

NONCLINICAL TOXICOLOGY

13.1 Carcinogenesis, Mutagenesis, Impairment of Fertility

Carcinogenesis

Carcinogenicity assessment has been conducted in mice, rats and p53(+/-) heterozygous mice. A slight but statistically significant increase in two common murine tumors, pulmonary and hepatic, was observed in an NMRI mouse carcinogenicity study, particularly in aged mice. Mice were dosed orally up to 30 mg/kg in the drinking water (0.5 times the maximum recommended daily human dosage or MRHD) for approximately two years, although the study was not done with the Maximum Tolerated Dose. This finding is not believed to suggest risk in humans.

No evidence of carcinogenicity was noted in a rat 2-year carcinogenicity study testing oral doses of up to 30 mg/kg in the drinking water (1 times the MRHD). In a second rat study, no evidence of carcinogenicity was noted in rats at oral doses up to 75 mg/kg/day for males and 100 mg/kg/day for females (approximately 2-fold the maximum recommended human daily dose MRHD) for two years. However, the excessive decrease in body weight gain observed in the rat study might have reduced their sensitivity to any potential carcinogenic effect of the drug. No carcinogenic effect of tramadol was observed in p53(+/–)-heterozygous mice at oral doses up to 150 mg/kg/day for 26 weeks.

Mutagenesis

Tramadol was mutagenic in the presence of metabolic activation in the mouse lymphoma assay. Tramadol was not mutagenic in the in vitro bacterial reverse mutation assay using Salmonella and E. coli (Ames), the mouse lymphoma assay in the absence of metabolic activation, the in vitro chromosomal aberration assay, or the in vivo micronucleus assay in bone marrow.

Impairment of Fertility

No effects on fertility were observed for tramadol at oral dose levels up to 50 mg/kg in male rats and 75 mg/kg in female rats. These dosages are 1.2 and 1.8 times the maximum recommended human daily dose based on body surface area, respectively.

PATIENT COUNSELING INFORMATION

Advise the patient to read the FDA-approved patient labeling (Medication Guide).

Storage and Disposal:

Because of the risks associated with accidental ingestion, misuse, and abuse, advise patients to store tramadol hydrochloride extended-release tablets securely, out of sight and reach of children, and in a location not accessible by others, including visitors to the home [see Warnings, Drug Abuse and Dependence]. Inform patients that leaving tramadol hydrochloride extended-release tablets unsecured can pose a deadly risk to others in the home.

Advise patients and caregivers that when medicines are no longer needed, they should be disposed of promptly. Inform patients that medicine take-back options are the preferred way to safely dispose of most types of unneeded medicines. If no take back programs or DEA-registered collectors are available, instruct patients to dispose of tramadol hydrochloride extended-release tablets by following these four steps:

Mix tramadol hydrochloride extended-release tablets (do not crush) with an unpalatable substance such as dirt, cat litter, or used coffee grounds;
Place the mixture in a container such as a sealed plastic bag;
Throw the container in the household trash;
Delete all personal information on the prescription label of the empty bottle

Inform patients that they can visit www.fda.gov/drugdisposal for additional information on disposal of unused medicines.

Addiction, Abuse, and Misuse

Inform patients that the use of tramadol hydrochloride extended-release tablets, even when taken as recommended, can result in addiction, abuse, and misuse, which can lead to overdose and death [see Warnings and Precautions (5.1)]. Instruct patients not to share tramadol hydrochloride extended-release tablets with others and to take steps to protect tramadol hydrochloride extended-release tablets from theft or misuse.

Life-Threatening Respiratory Depression

Inform patients of the risk of life-threatening respiratory depression, including information that the risk is greatest when starting tramadol hydrochloride extended-release tablets or when the dosage is increased, and that it can occur even at recommended dosages [see Warnings and Precautions (5.3)]. Advise patients how to recognize respiratory depression and to seek medical attention if breathing difficulties develop.

Accidental Ingestion

Inform patients that accidental ingestion, especially by children, may result in respiratory depression or death [see Warnings and Precautions (5.3)]. Instruct patients to take steps to store tramadol hydrochloride extended-release tablets securely and to dispose of unused tramadol hydrochloride extended-release tablets in accordance with the local state guidelines and/or regulations.

Ultra-Rapid Metabolism of Tramadol and Other Risk Factors for Life-threatening Respiratory Depression in Children

Advise caregivers that tramadol hydrochloride extended-release tablets are contraindicated in children younger than 12 years of age and in children younger than 18 years of age following tonsillectomy and/or adenoidectomy. Advise caregivers of children 12 to 18 years of age receiving tramadol hydrochloride extended-release tablets to monitor for signs of respiratory depression [see Warnings and Precautions (5.4)].

Interactions with Benzodiazepines and Other CNS Depressants

Inform patients and caregivers that potentially fatal additive effects may occur if tramadol hydrochloride extended-release tablets are used with benzodiazepines or other CNS depressants, including alcohol, and not to use these concomitantly unless supervised by a healthcare provider [see Warnings and Precautions (5.7), Drug Interactions (7)].

Serotonin Syndrome

Inform patients that tramadol could cause a rare but potentially life-threatening condition, particularly during concomitant use with serotonergic drugs. Warn patients of the symptoms of serotonin syndrome and to seek medical attention right away if symptoms develop. Instruct patients to inform their healthcare provider if they are taking, or plan to take serotonergic medications [see Warnings and Precautions (5.8), Drug Interactions (7)].

Seizures

Inform patients that tramadol hydrochloride extended-release tablets may cause seizures with concomitant use of serotonergic agents (including SSRIs, SNRIs, and triptans) or drugs that significantly reduce the metabolic clearance of tramadol [see Warnings and Precautions (5.9)].

MAOI Interaction

Inform patients not to take tramadol hydrochloride extended-release tablets while using any drugs that inhibit monoamine oxidase. Patients should not start MAOIs while taking tramadol hydrochloride extended-release tablets [see Drug Interactions (7)].

Adrenal Insufficiency

Inform patients that opioids could cause adrenal insufficiency, a potentially life-threatening condition. Adrenal insufficiency may present with non-specific symptoms and signs such as nausea, vomiting, anorexia, fatigue, weakness, dizziness, and low blood pressure. Advise patients to seek medical attention if they experience a constellation of these symptoms [see Warnings and Precautions (5.11)].

Important Administration Instructions

Instruct patients how to properly take tramadol hydrochloride extended-release tablets, including the following:

Tramadol hydrochloride extended-release tablets are designed to work properly only if swallowed intact. Taking cut, broken, chewed, crushed, or dissolved tramadol hydrochloride extended-release tablets can result in a fatal overdose [see Dosage and Administration (2.1)].
Advise patients not to exceed the single-dose and 24-hour dose limit and the time interval between doses, since exceeding these recommendations can result in respiratory depression, seizures, hepatic toxicity, and death. [see Dosage and Administration (2.1)].
Do not discontinue tramadol hydrochloride extended-release tablets without first discussing the need for a tapering regimen with the prescriber [see Dosage and Administration (2.4)] .

Important Discontinuation Instructions

In order to avoid developing withdrawal symptoms, instruct patients not to discontinue tramadol hydrochloride extended-release tablets without first discussing a tapering plan with the prescriber [see Dosage and Administration]

Hypotension

Inform patients that tramadol hydrochloride extended-release tablets may cause orthostatic hypotension and syncope. Instruct patients how to recognize symptoms of low blood pressure and how to reduce the risk of serious consequences should hypotension occur (e.g., sit or lie down, carefully rise from a sitting or lying position) [see Warnings and Precautions (5.13)].

Anaphylaxis

Inform patients that anaphylaxis has been reported with ingredients contained in tramadol hydrochloride extended-release tablets. Advise patients how to recognize such a reaction and when to seek medical attention [see Contraindications (4), Warnings and Precautions (5.16), Adverse Reactions (6)].

Pregnancy

Neonatal Opioid Withdrawal Syndrome

Inform female patients of reproductive potential that prolonged use of tramadol hydrochloride extended-release tablets during pregnancy can result in neonatal opioid withdrawal syndrome, which may be life-threatening if not recognized and treated [see Warnings and Precautions (5.5), Use in Specific Populations (8.1)].

Embryo-Fetal Toxicity

Inform female patients of reproductive potential that tramadol hydrochloride extended-release tablets can cause fetal harm and to inform their healthcare provider of a known or suspected pregnancy [see Use in Specific Populations (8.1)].

Lactation

Advise women that breastfeeding is not recommended during treatment with tramadol hydrochloride extended-release tablets [see Use in Specific Populations (8.2)].

Infertility

Inform patients that chronic use of opioids may cause reduced fertility. It is not known whether these effects on fertility are reversible [see Adverse Reactions (6.2), Use in Specific Populations (8.3)].

Driving or Operating Heavy Machinery

Inform patients that tramadol hydrochloride extended-release tablets may impair the ability to perform potentially hazardous activities such as driving a car or operating heavy machinery. Advise patients not to perform such tasks until they know how they will react to the medication [see Warnings and Precautions (5.18)].

Constipation

Advise patients of the potential for severe constipation, including management instructions and when to seek medical attention [see Adverse Reactions (6), Clinical Pharmacology (12.1)].

Manufactured for:

Lupin Pharmaceuticals, Inc.

Baltimore, Maryland 21202

United States

Manufactured by:

Lupin Limited

Pithampur (M.P.) - 454 775

INDIA

Revised: May 08, 2019 ID#: 260434

Medication Guide

Tramadol Hydrochloride Extended-Release Tablets , CIV

(tram' a dol hye'' droe klor' ide)

Tramadol hydrochloride extended-release tablets are:

A strong prescription pain medicine that contains an opioid (narcotic) that is used to manage pain severe enough to require daily around-the-clock, long-term treatment with an opioid, when other pain treatments such as non-opioid pain medicines or immediate-release opioid medicines do not treat your pain well enough or you cannot tolerate them.
A long-acting (extended-release) opioid pain medicine that can put you at risk for overdose and death. Even if you take your dose correctly as prescribed you are at risk for opioid addiction, abuse, and misuse that can lead to death.
Not for use to treat pain that is not around-the-clock.

Important information about tramadol hydrochloride extended-release tablets:

Get emergency help right away if you take too much tramadol hydrochloride extended-release tablets (overdose) . When you first start taking tramadol hydrochloride extended-release tablets, when your dose is changed, or if you take too much (overdose), serious or life-threatening breathing problems that can lead to death may occur.
Taking tramadol hydrochloride extended-release tablets with other opioid medicines, benzodiazepines, alcohol, or other central nervous system depressants (including street drugs) can cause severe drowsiness, decreased awareness, breathing problems, coma, and death.
Never give anyone else your tramadol hydrochloride extended-release tablets. They could die from taking it. Selling or giving away tramadol hydrochloride extended-release tablets is against the law.
Store tramadol hydrochloride extended-release tablets securely, out of sight and reach of children, and in a location not accessible by others, including visitors to the home.

Important Information Guiding Use in Pediatric Patients:

Do not give tramadol hydrochloride extended-release tablets to a child younger than 12 years of age.
Do not give tramadol hydrochloride extended-release tablets to a child younger than 18 years of age after surgery to remove the tonsils and/or adenoids.
Avoid giving tramadol hydrochloride extended-release tablets to children between 12 to 18 years of age who have risk factors for breathing problems such as obstructive sleep apnea, obesity, or underlying lung problems.

Do not take tramadol hydrochloride extended-release tablets if you have:

severe asthma, trouble breathing, or other lung problems.
a bowel blockage or have narrowing of the stomach or intestines.

Before taking tramadol hydrochloride extended-release tablets, tell your healthcare provider if you have a history of:

head injury, seizures
problems urinating
abuse of street or prescription drugs, alcohol addiction, or mental health problems.
liver, kidney, thyroid problems
pancreas or gallbladder problems

Tell your healthcare provider if you are:

pregnant or planning to become pregnant . Prolonged use of tramadol hydrochloride extended-release tablets during pregnancy can cause withdrawal symptoms in your newborn baby that could be life-threatening if not recognized and treated.
breastfeeding . Not recommended-: it may harm your baby.
taking prescription or over-the-counter medicines, vitamins, or herbal supplements. Taking tramadol hydrochloride extended-release tablets with certain other medicines can cause serious side effects that could lead to death.

When taking tramadol hydrochloride extended-release tablets:

Do not change your dose. Take tramadol hydrochloride extended-release tablets exactly as prescribed by your healthcare provider. Use the lowest dose possible for the shortest time needed.
Take your prescribed dose once a day at the same time every day. Do not take more than your prescribed dose. If you miss a dose, take your next dose at your usual time.
Swallow tramadol hydrochloride extended-release tablets whole. Do not cut, break, chew, crush, dissolve, snort, or inject tramadol hydrochloride extended-release tablets because this may cause you to overdose and die.
Call your healthcare provider if the dose you are taking does not control your pain.
Do not stop taking tramadol hydrochloride extended-release tablets without talking to your healthcare provider.
Dispose of expired, unwanted, or unused tramadol hydrochloride extended-release tablets by taking your drug to an authorized DEA-registered collector or drug take-back program. If one is not available, you can dispose of tramadol hydrochloride extended-release tablets by mixing the product with dirt, cat litter, or coffee grounds; placing the mixture in a sealed plastic bag, and throwing the bag in your trash.

While taking tramadol hydrochloride extended-release tablets DO NOT:

Drive or operate heavy machinery, until you know how tramadol hydrochloride extended-release tablet affects you. Tramadol hydrochloride extended-release tablets can make you sleepy, dizzy, or lightheaded.
Drink alcohol or use prescription or over-the-counter medicines that contain alcohol. Using products containing alcohol during treatment with tramadol hydrochloride extended-release tablets may cause you to overdose and die.

The possible side effects of tramadol hydrochloride extended-release tablets:

constipation, nausea, sleepiness, vomiting, tiredness, headache, dizziness, abdominal pain, seizure. Call your healthcare provider if you have any of these symptoms and they are severe.

Get emergency medical help if you have:

trouble breathing, shortness of breath, fast heartbeat, chest pain, swelling of your face, tongue, or throat, extreme drowsiness, light-headedness when changing positions, feeling faint, agitation, high body temperature, trouble walking, stiff muscles, or mental changes such as confusion.

These are not all the possible side effects of tramadol hydrochloride extended-release tablets. Call your doctor for medical advice about side effects. You may report side effects to FDA at 1-800-FDA-1088. For more information go to dailymed.nlm.nih.gov or www.lupinpharmaceuticals.com or call Lupin Pharmaceuticals, Inc. at 1-800-399-2561.

This Medication Guide has been approved by the U.S. Food and Drug Administration.

Manufactured for:

Lupin Pharmaceuticals, Inc.

Baltimore, Maryland 21202

United States

Manufactured by:

Lupin Limited

Pithampur (M.P.) - 454 775

INDIA

Revised: May 08, 2019 ID#: 260433